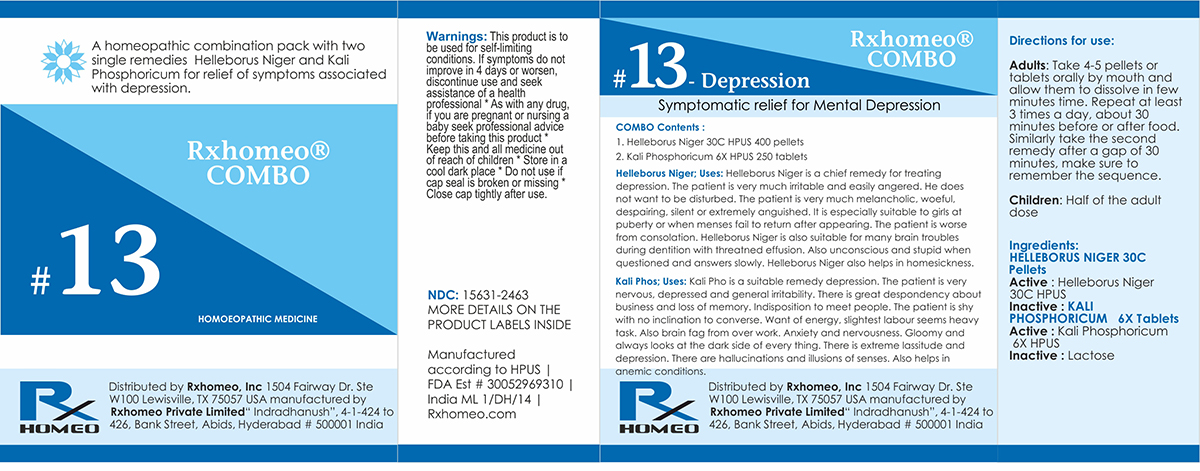 DRUG LABEL: Rxhomeo Homeopathic Combo 13
NDC: 15631-2463 | Form: KIT | Route: ORAL
Manufacturer: Rxhomeo Private Limited d.b.a.
Category: homeopathic | Type: HUMAN OTC DRUG LABEL
Date: 20161023

ACTIVE INGREDIENTS: HELLEBORUS NIGER ROOT 3 [hp_X]/1 1; POTASSIUM PHOSPHATE, DIBASIC 1 [hp_X]/1 1
INACTIVE INGREDIENTS: SUCROSE; LACTOSE

ACTIVE INGREDIENT

HELLEBORUS NIGER HPUS 3X and higher

KALI PHOSPHORICUM HPUS 1X and higher

USES

A homeopathic combination pack with two single remedies Helleborus Niger and Kali Phosphoricum for relief of symptoms associated with depression.

Helleborus Niger: Helleborus Niger is a chief remedy for treating depression. The patient is very much irritable and easily angered. He does not want to be disturbed. The patient is very much melancholic, woeful, despairing, silent or extremely anguished. It is especially suitable to girls at puberty or when menses fail to return after appearing. The patient is worse from consolation. Helleborus Niger is also suitable for many brain troubles during dentition with threatned effusion. Also unconscious and stupid when questioned and answers slowly. Helleborus Niger also helps in homesickness.

Kali Phos: Kali Pho is a suitable remedy depression. The patient is very nervous, depressed and general irritability. There is great despondency about business and loss of memory. Indisposition to meet people. The patient is shy with no inclination to converse. Want of energy, slightest labour seems heavy task. Also brain fag from over work. Anxiety and nervousness. Gloomy and always looks at the dark side of everything. There is extreme lassitude and depression. There are hallucinations and illusions of senses. Also helps in anemic conditions.

INDICATIONS

Condition listed above or as directed by the physician

DOSAGE

Adults: Take 4-5 pellets or tablets orally by mouth and allow them to dissolve on tongue. Repeat at least 3 times a day, about 30 minutes before or after food. Similarly take the second remedy after a gap of 30 minutes, make sure to remember the sequence.

Children: Half of the adult dose.

WARNINGS

This product is to be used for self-limiting conditions

STOP USE

If symptoms do not improve in 4 days, or worsen, discontinue use and seek assistance of health professional

KEEP OUT OF REACH OF CHILDREN

Keep this and all medication out of reach of children

Do not use if capseal is broken or missing.

Close the cap tightly after use.

INACTIVE INGREDIENTS

Sucrose for Pellets.

Lactose for Tablets.

STORAGE

Store in a cool dark place

QUESTIONS OR COMMENTS

www.Rxhomeo.com | 1.888.2796642 | info@rxhomeo.com
Rxhomeo, Inc 1504 Fairway Dr. Ste W 100 Lewisville, TX 75057 USA